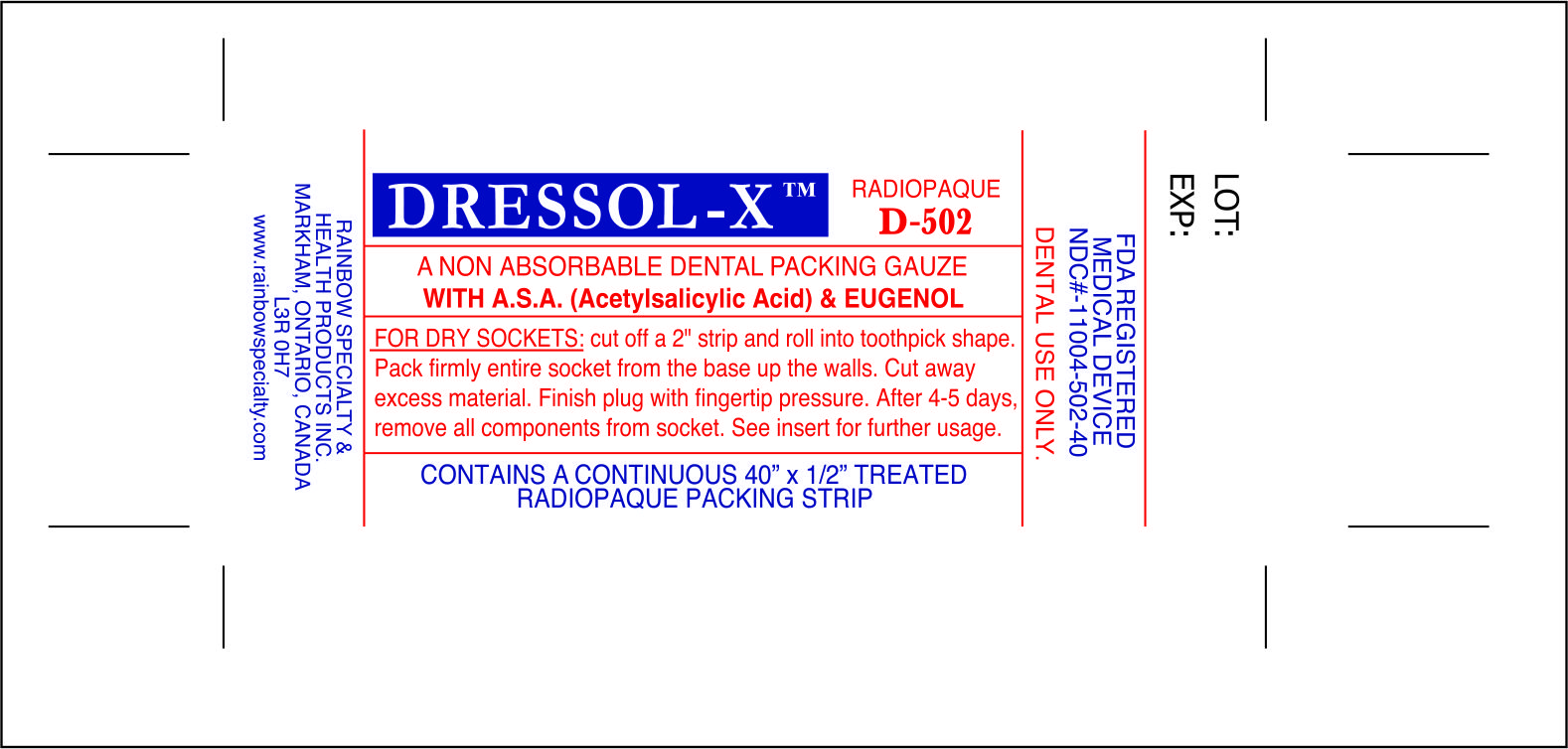 DRUG LABEL: Dressol-X
NDC: 11004-502 | Form: DRESSING
Manufacturer: Rainbow Specialty & Health Products, Inc.
Category: other | Type: MEDICAL DEVICE
Date: 20111213

ACTIVE INGREDIENTS: ASPIRIN 115 mg/1 1; EUGENOL 80 mg/1 1
INACTIVE INGREDIENTS: PARAFFIN; MINERAL OIL

ACTIVE INGREDIENT

A Non Absorbable Dental Packing Gauze With A.S.A. (Acetylsalicylic Acid) and Eugenol

INDICATIONS AND USAGE

For Dry Sockets: cut off a 2" strip and roll into toothpick shape. Pack firmly entire socket from the base up the walls. Cut away excess material. Finish plug with fingertip pressure. After 4-5 days, remove all components from socket. See insert for further usage.